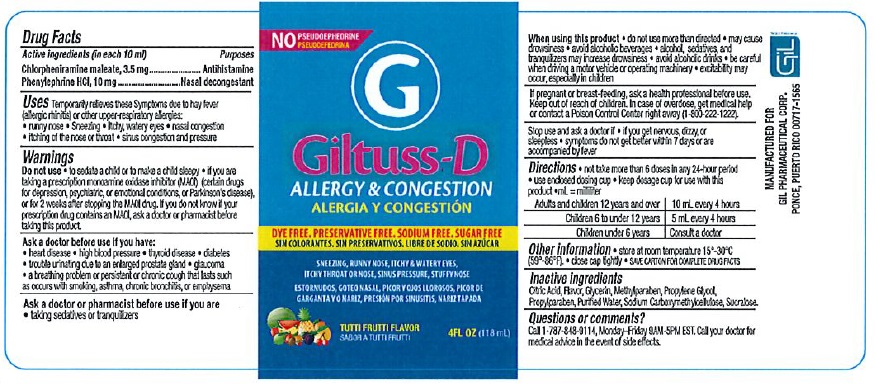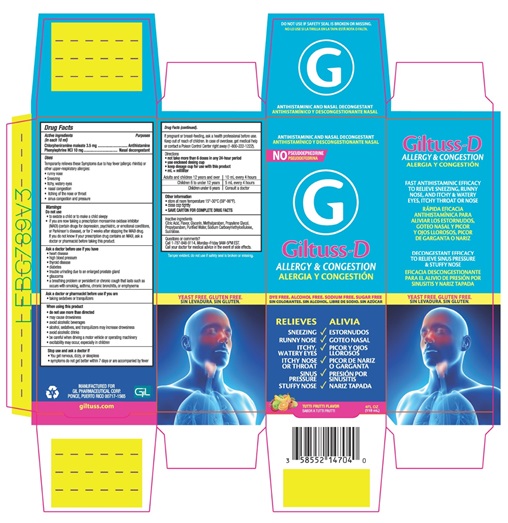 DRUG LABEL: Giltuss D
NDC: 58552-147 | Form: SYRUP
Manufacturer: Gil Pharmaceutical Corp
Category: otc | Type: HUMAN OTC DRUG LABEL
Date: 20260212

ACTIVE INGREDIENTS: CHLORPHENIRAMINE MALEATE 3.5 mg/1 1; PHENYLEPHRINE HYDROCHLORIDE 10 mg/1 1
INACTIVE INGREDIENTS: CITRIC ACID ACETATE; GLYCERIN; METHYLPARABEN; PROPYLENE GLYCOL; PROPYLPARABEN; WATER; CARBOXYMETHYLCELLULOSE SODIUM; SUCRALOSE

Giltuss-D
ALLERGY & CONGESTION
ANTIHISTAMINIC AND NASAL DECONGESTANT

Drug Facts

Active ingredients (in each 10 mL) Purpose

Chlorpheniramine maleate 3.5 mg .... Antihistamine

Phenylephrine HCl 10 mg ................ Nasal decongestant

Uses

Temporarily relieves these Symptoms due to hay fever (allergic rhinitis) or other upper-respiratory allergies:

- runny nose
- Sneezing
- Itchy, watery eyes
- nasal congestion
- itching of the nose or throat
- sinus congestion and pressure

Warnings

Do not use

- to sedate a child or to make a child sleepy
- if you are now taking a prescription monoamine oxidase inhibitor (MAOI) (certain drugs for depression, psychiatric, or emotional conditions, or Parkinson's disease), or for 2 weeks after stopping the MAOI drug.
  If you do not know if your prescription drug contains an MAOI, ask a doctor or pharmacist before taking this product.

Ask a doctor before use if you have

- heart disease
- high blood pressure
- thyroid disease
- diabetes
- trouble urinating due to an enlarged prostate gland
- glaucoma
- a breathing problem or persistent or chronic cough that lasts such as occurs with smoking, asthma, chronic bronchitis, or emphysema

Ask a doctor or pharmacist before use if you are

- taking sedatives or tranquilizers

When using this product

- do not use more than directed
- may cause drowsiness
- avoid alcoholic beverages
- alcohol, sedatives, and tranquilizers may increase drowsiness
- avoid alcoholic drinks
- be careful when driving a motor vehicle or operating machinery
- excitability may occur, especially in children

Stop use and ask a doctor if

- You get nervous, dizzy, or sleepless
- symptoms do not get better within 7 days or are accompanied by fever

PREGNANCY OR BREAST FEEDING

If pregnant or breast-feeding, ask a health professional before use.
Keep out of reach of children. In case of overdose, get medical help or contact a Poison Control Center right away (1-800-222-1222).

Directions

- not take more than 6 doses in any 24-hour period
- use enclosed dosing cup
- keep dosage cup for use with this product
- mL = milliliter

Adults and children 12 years and over | 10 mL every 4 hours
Children 6 to under 12 years | 5 mL every 4 hours
Children under 6 years | Consult a doctor

Other information

- store at room temperature 15°-30°C (59°-86°F)
- close cap tightly
- SAVE CARTON FOR COMPLETE DRUG FACTS

Inactive ingredients

Citric Acid, Flavor, Glycerin, Methylparaben, Propylene Glycol, Propylparaben, Purified Water, Sodium Carboxymethylcellulose, Sucralose.

Questions or comments?

Call 1-787-848-9114, Monday-Friday 9AM-5PM EST. Call your doctor for medical advice in the event of side effects.

Label revised: 04/24

MANUFACTURED FOR
GIL PHARMACEUTICAL CORP.
PONCE, PUERTO RICO 00717-1565

PRINCIPAL DISPLAY PANEL

Giltuss-D ALLERGY & CONGESTION - NDC 58552-147-04 - Bottle Label

Giltuss-D ALLERGY & CONGESTION - NDC 58552-147-04 - Carton Label